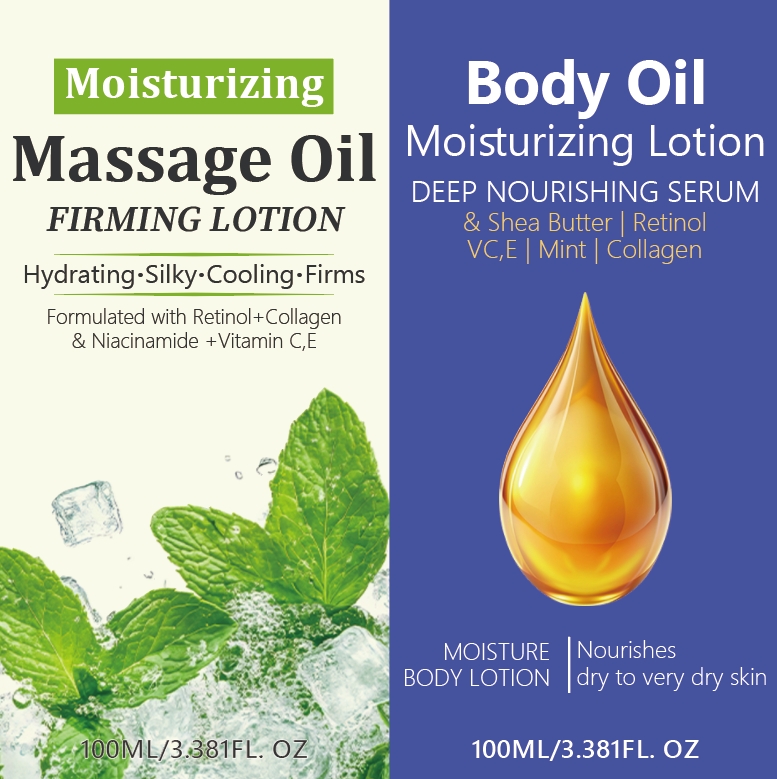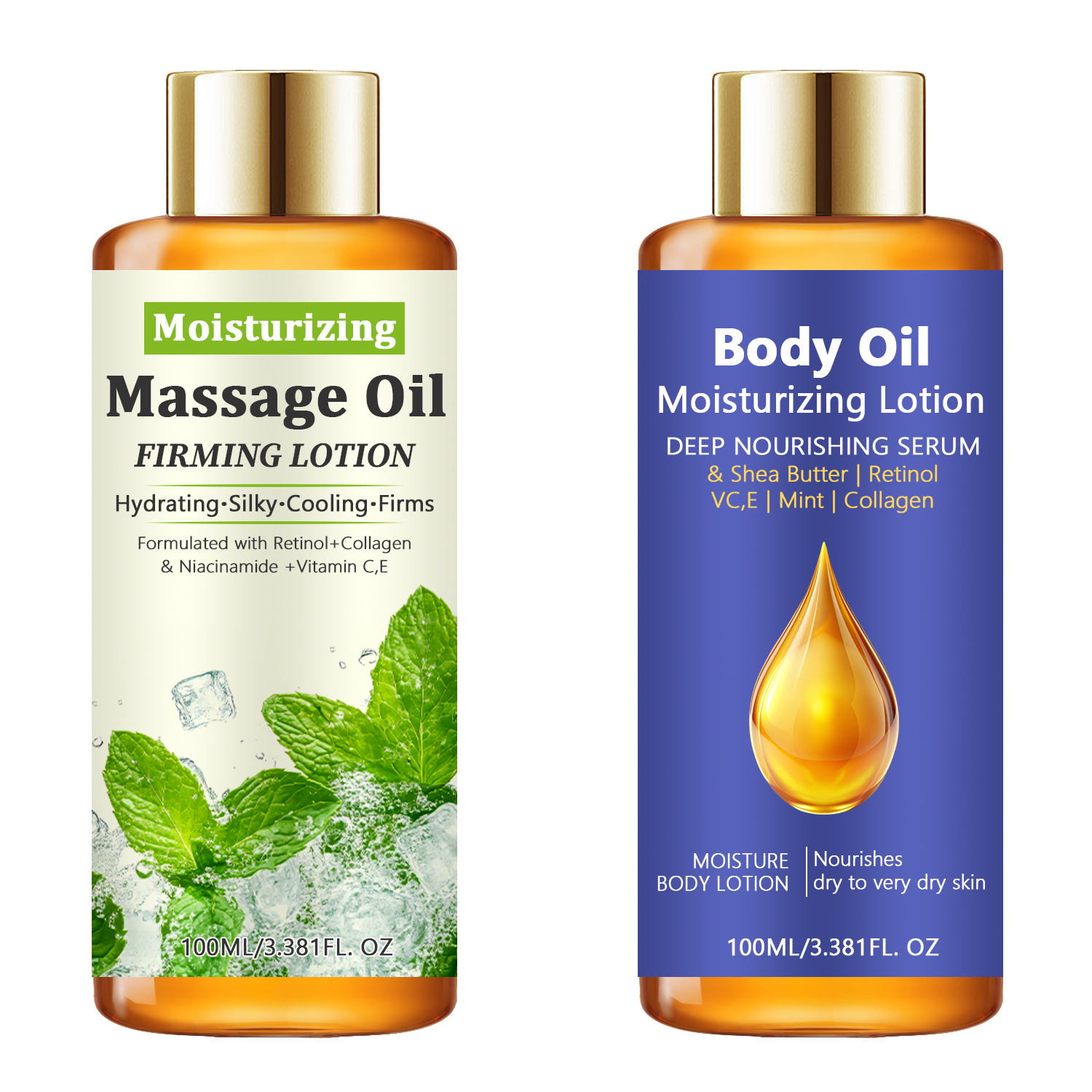 DRUG LABEL: Moisturizing Massage Oil
NDC: 84025-221 | Form: OIL
Manufacturer: Guangzhou Yanxi Biotechnology Co., Ltd
Category: otc | Type: HUMAN OTC DRUG LABEL
Date: 20241018

ACTIVE INGREDIENTS: GLYCERIN 5 mg/100 mL; HYALURONIC ACID 3 mg/100 mL
INACTIVE INGREDIENTS: WATER

DOSAGE AND ADMINISTRATION

Dispense oil on your palms.
Gently rub your palms together to warm the oil.
Massage oil onto sore muscles until absorb.

WARNINGS

Keep out of children

INACTIVE INGREDIENT

Aqua

INDICATIONS AND USAGE

for dry skin and sensitive skin.

keep out of children

PURPOSE

Peppermint oil has properties that have been found to relieve muscle spasms and to release deep muscle tension. Because it contains menthol, peppermint has a cooling effect on sore, achy muscles. A little bit of Peppermint Massage Oil goes a long way on your body, and you will be feeling relaxed and rejuvenated in no time.